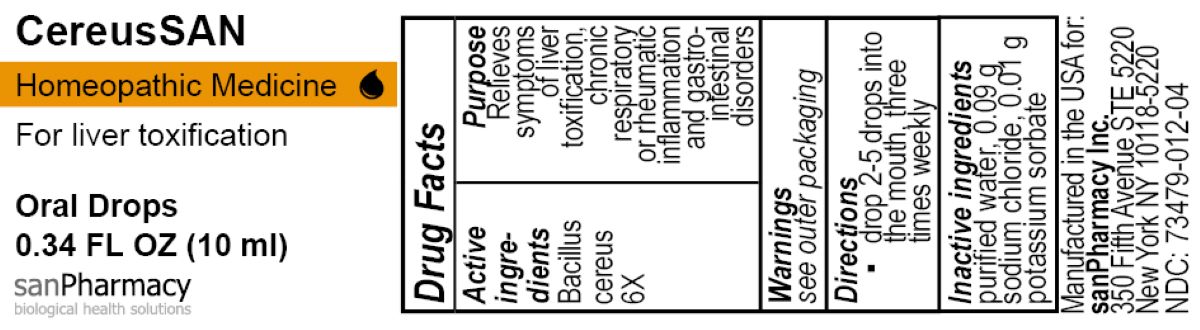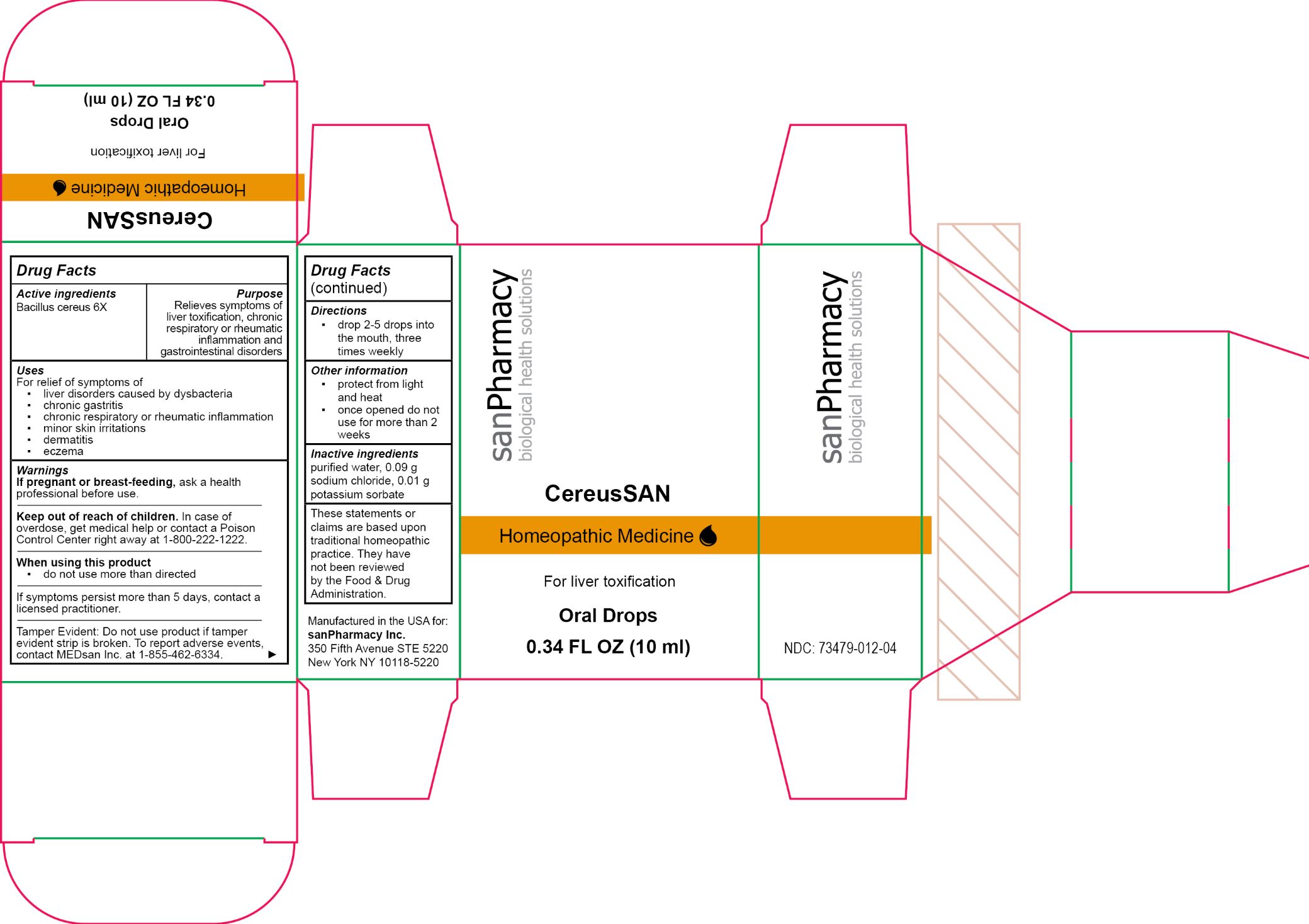 DRUG LABEL: CereusSAN
NDC: 73479-012 | Form: SOLUTION/ DROPS
Manufacturer: sanPharmacy Inc.
Category: homeopathic | Type: HUMAN OTC DRUG LABEL
Date: 20240424

ACTIVE INGREDIENTS: BACILLUS CEREUS 6 [hp_X]/10 mL
INACTIVE INGREDIENTS: POTASSIUM SORBATE 0.01 g/10 mL; WATER 10 mL/10 mL; SODIUM CHLORIDE 0.09 g/10 mL

CereusSAN Drops

Indications

For liver toxification

PURPOSE

Relieves symptoms of liver toxification, chronic respiratory or rheumatic inflammation and gastrointestinal disorders

Dosage

drop 2-5 drops into the mouth, three times weekly

Ingredients

Bacillus cereus 6X

INACTIVE INGREDIENT

purified water, 0.09 g sodium chloride, 0.01 g potassium sorbate

Warnings

If pregnant or breast-feeding, ask a health professional before use.
______________________________
Keep out of reach of children. In case of overdose, get medical help or contact a Poison Control Center right away at 1-800-222-1222.
______________________________
When using this product
▪ do not use more than directed
______________________________
If symptoms persist more than 5 days, contact a licensed practitioner.
______________________________
Tamper Evident: Do not use product if tamper evident strip is broken. To report adverse events, contact MEDsan Inc. at 1-855-462-6334.

Keep out of reach of children. In case of overdose, get medical help or contact a Poison Control Center right away at 1-800-222-1222

Tamper Evident

Tamper Evident: Do not use product if tamper evident strip is broken. To report adverse events, contact MEDsan Inc. at 1-855-462-6334

Manufactured in the USA for:
sanPharmacy Inc.
350 Fifth Avenue STE 5220
New York NY 10118-5220

Liability statement

These statements or claims are based upon traditional homeopathic practice. They have not been reviewed by the Food & Drug Administration.

STORAGE AND HANDLING

protect from light and heat

once opened do not use for more than 2 weeks

PACKAGE LABEL

CereusSAN

Homeopathic Medicine

For liver toxification

Oral Drops

0.34 FL OZ (10 ml)

sanPharmacy

biological health solutions